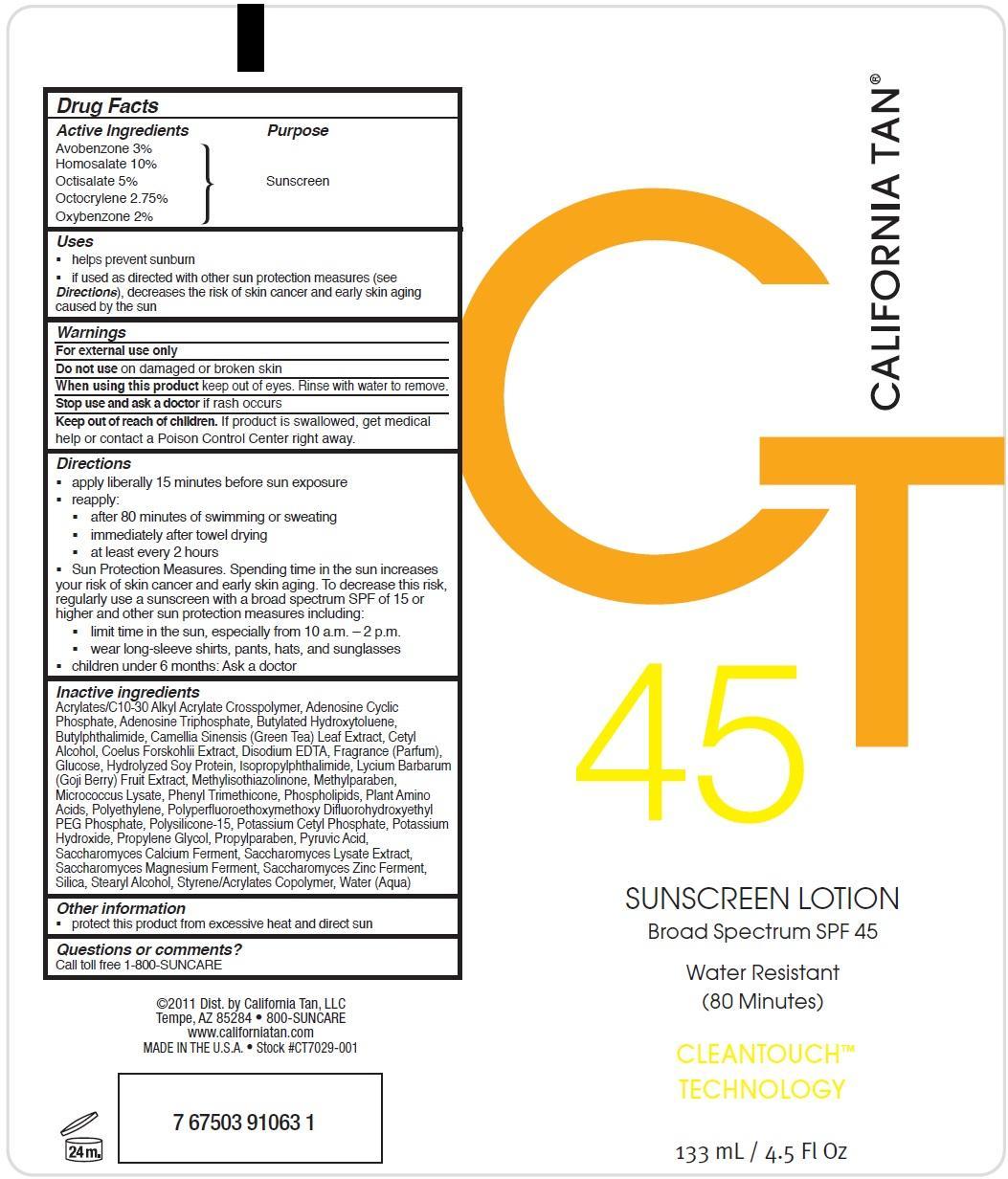 DRUG LABEL: California Tan
NDC: 58443-0097 | Form: LOTION
Manufacturer: Prime Enterprises, Inc.
Category: otc | Type: HUMAN OTC DRUG LABEL
Date: 20200117

ACTIVE INGREDIENTS: AVOBENZONE 29.9 mg/1 mL; HOMOSALATE 99.8 mg/1 mL; OCTISALATE 49.9 mg/1 mL; OCTOCRYLENE 27.5 mg/1 mL; OXYBENZONE 19.9 mg/1 mL
INACTIVE INGREDIENTS: POLYSILICONE-15; POTASSIUM CETYL PHOSPHATE; POTASSIUM HYDROXIDE; PROPYLENE GLYCOL; PROPYLPARABEN; PYRUVIC ACID; CALCIUM; SACCHAROMYCES LYSATE; MAGNESIUM; ZINC; SILICON DIOXIDE; STEARYL ALCOHOL; STYRENE; WATER; CARBOMER COPOLYMER TYPE A (ALLYL PENTAERYTHRITOL CROSSLINKED); ADENOSINE CYCLIC PHOSPHATE; ADENOSINE TRIPHOSPHATE; BUTYLATED HYDROXYTOLUENE; 3-BUTYLPHTHALIDE; GREEN TEA LEAF; CETYL ALCOHOL; PLECTRANTHUS BARBATUS ROOT; EDETATE DISODIUM; DEXTROSE; SOY PROTEIN; ISOPROPYLPHTHALIMIDE; LYCIUM BARBARUM FRUIT; METHYLISOTHIAZOLINONE; METHYLPARABEN; PHENYL TRIMETHICONE; HIGH DENSITY POLYETHYLENE; OMEGA-3 FATTY ACIDS; AMINO ACIDS

Active ingredients

Avobenzone 3 %, Homosalate 10 %, Octisalate 5 %, Octocrylene 2.7 %, and Oxybenzone 2 %

Purpose

Sunscreen

Uses

- helps prevent sunburn
- if used as directed with other sun protection measures (see Directions), decreases the risk of skin cancer and early skin aging caused by the sun

Warnings

OTHER SAFETY INFORMATION

For external use only

Do not use on damaged or broken skin.

When using this product keep out of eyes. Rinse with water to remove.

Stop use and ask a doctor if rash occurs.

Keep out of reach of children. If product is swallowed, get medical help or contact a Poison Control Center right away.

Directions

- apply liberally 15 minutes before sun exposure
- reapply:
  - after 80 minutes of swimming or sweating
  - immediately after towel drying
  - at least every 2 hours
- Sun Protection Measures. Spending time in the sun increases your risk of skin cancer and early skin aging. To decrease this risk, regularly use a sunscreen with a broad spectrum SPF of 15 or higher and other sun protection measures including:
  - limit time in the sun especially from 10 a.m. – 2 p.m.
  - wear long-sleeve shirts, pants, hats, and sunglasses
- children under 6 months: Ask a doctor

Inactive Ingredients

Acrylates/C10-30 Alkyl Acrylate Crosspolymer, Adenosine Cyclic Phosphate, Adenosine Triphosphate, Butylated Hydroxytoluene, Butylphthalimide, Camellia Sinensis (Green Tea) Leaf Extract, Cetyl Alcohol, Coelus Forskohlii Extract, Disodium EDTA, Fragrance (Parfum), Glucose, Hydrolyzed Soy Protein, Isopropylphthalimide, Lycium Barbarum (Goji Berry) Fruit Extract, Methylisothiazolinone, Methylparaben, Micrococcus Lysate, Phenyl Trimethicone, Phospholipids, Plant Amino Acids, Polyethylene, Polyperfluoroethoxymethoxy Difluorohydroxyethyl PEG Phosphate, Polysilicone-15, Potassium Cetyl Phosphate, Potassium Hydroxide, Propylene Glycol, Propylparaben, Pyruvic Acid, Saccharomyces Calcium Ferment, Saccharomyces Lysate Extract, Saccharomyces Magnesium Ferment, Saccharomyces Zinc Ferment, Silica, Stearyl Alcohol, Styrene/Acrylates Copolymer, Water (Aqua)

Other information

- protect this product from excesive heat and direct sun

Questions or Comments?

Call toll free 1-800-SUNCARE

PRINCIPAL DISPLAY PANEL - 133 mL Tube Label

CALIFORNIA TAN

CT

45

SUNSCREEN LOTION

Broad Spectrum SPF 45

Water Resistant

(80 Minutes)

CLEANTOUCH

TECHNOLOGY

133 mL / 4.5 Fl Oz